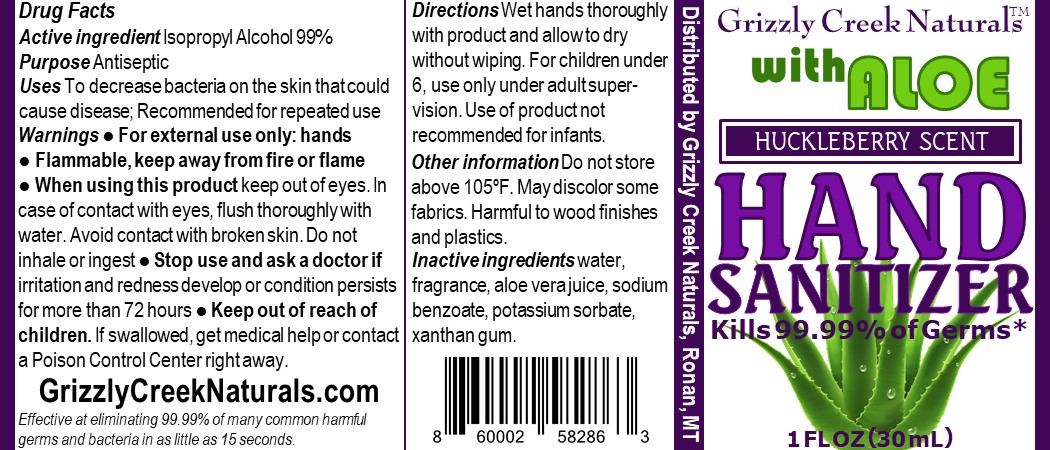 DRUG LABEL: Grizzly Creek Naturals Hand Sanitizer
NDC: 73816-101 | Form: LIQUID
Manufacturer: BLACK BIRD POTENTIALS INC.
Category: otc | Type: HUMAN OTC DRUG LABEL
Date: 20200327

ACTIVE INGREDIENTS: ISOPROPYL ALCOHOL 0.7 mL/1 mL
INACTIVE INGREDIENTS: ALOE ARBORESCENS LEAF; XANTHAN GUM; WATER; SODIUM BENZOATE; POTASSIUM SORBATE; VACCINIUM MYRTILLUS ANTHOCYANOSIDES

DRUG FACTS

Active ingredient Isopropyl Alcohol 99%

Purpose Antiseptic

DRUG FACTS

Active ingredient Isopropyl Alcohol 99%

Purpose Antiseptic

Uses

To decrease bacteria on the skin that could

cause disease; Recommended for repeated use

Warnings

● For external use only: hands ● Flammable, keep away from fire or flame ● When using this product keep out of eyes. In

case of contact with eyes, flush thoroughly with water. Avoid contact with broken skin. Do not inhale or ingest

Stop use and ask a doctor if irritation and redness develop or condition persists for more than 72 hours

Keep out of reach of children. If swallowed, get medical help or contact a Poison Control Center right away.

Directions

Wet hands thoroughly with product and allow to dry without wiping. For children under 6, use only under adult super-vision. Use of product not recommended for infants.

Other information

Do not store above 105ºF. May discolor some fabrics. Harmful to wood finishes and plastics.

Inactive ingredients

water, fragrance, aloe vera juice, sodium benzoate, potassium sorbate, xanthan gum.

Directions

Wet hands thoroughly with product and allow to dry without wiping. For children under 6, use only under adult super-vision. Use of product not recommended for infants.

Uses

To decrease bacteria on the skin that could cause disease; Recommended for repeated use

PACKAGE LABEL

30 mL NDC: 73816-101- 01